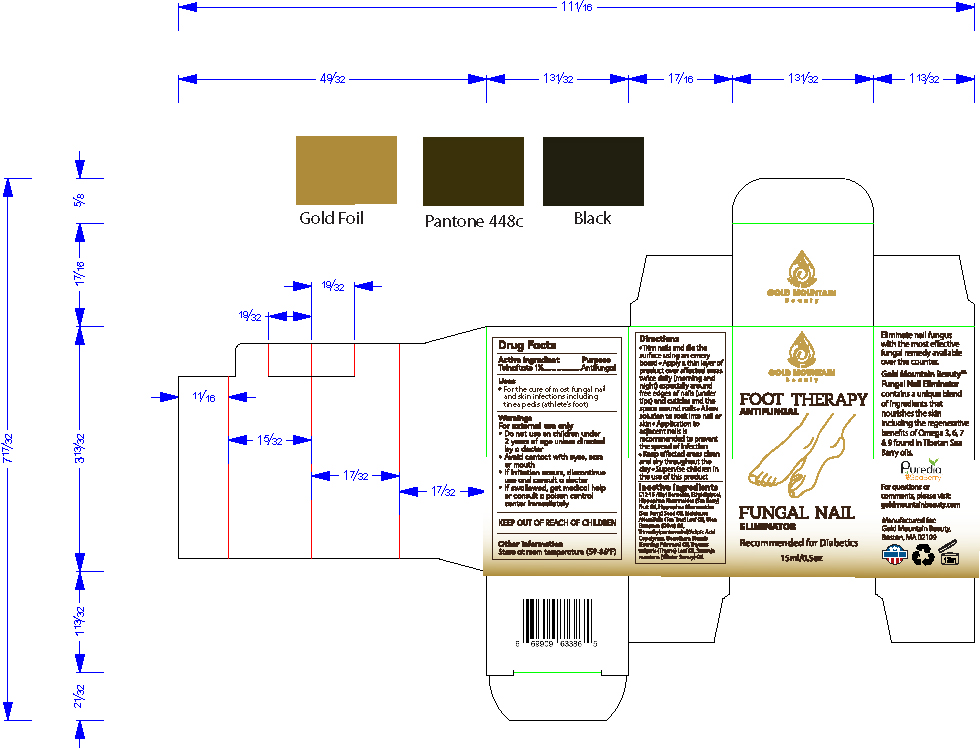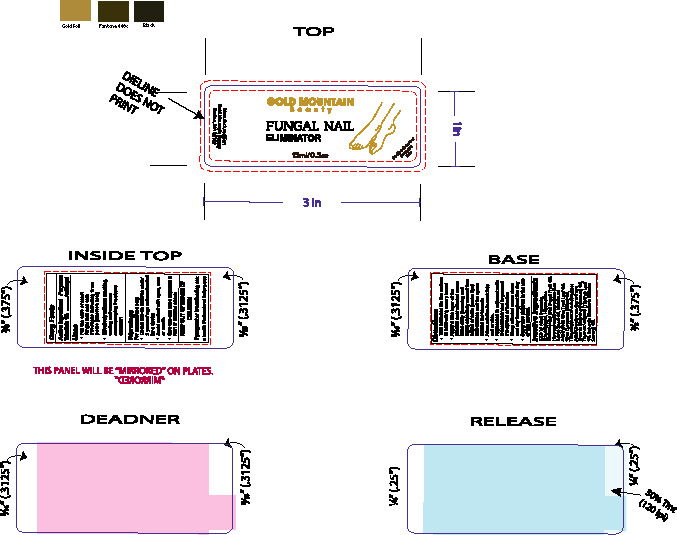 DRUG LABEL: Gold Mountain Beauty Fungal Nail Eliminator
NDC: 76348-417 | Form: OIL
Manufacturer: Renu Laboratories, Inc.
Category: otc | Type: HUMAN OTC DRUG LABEL
Date: 20220114

ACTIVE INGREDIENTS: TOLNAFTATE 0.14 g/14 g
INACTIVE INGREDIENTS: THYME OIL; EVENING PRIMROSE OIL; WINTER SAVORY OIL; TRIMETHYLPENTANEDIOL/ADIPIC ACID/GLYCERIN CROSSPOLYMER (25000 MPA.S); OLIVE OIL; HIPPOPHAE RHAMNOIDES FRUIT OIL; DIETHYLENE GLYCOL MONOETHYL ETHER; ALKYL (C12-15) BENZOATE; TEA TREE OIL; HIPPOPHAE RHAMNOIDES SEED OIL

Gold Mountain Beauty Fungal Nail Eliminator

Active Ingredient

Tolnaftate 1%

Purpose

Antifungal

For external use only

- Do not use on children under 2 years of age unless directed by a doctor
- Avoid contact with eyes, ears or mouth
- If irritation occurs, discontinue use and consult a doctor
- If swallowed, get medical help or consult a poison control center immediately

KEEP OUT OF REACH OF CHILDREN

Other information

Store at room temperature (59 - 86 degrees F)

Inactive ingredients

C12-15 Alkyl Benzoate, Ethyldiglycol, Hippophae Rhamnoides (Sea Berry) Fruit Oil, Hippophae Rhamnoides (Sea Berry) Seed Oil, Melaleuca Alternifolia (Tea Tree) Leaf Oil, Olea Europaea (Olive) Oil, Trimethylpentanediol/Adipic Acid Copolymer

ASK DOCTOR

- If irritation occurs, discontinue use and consult a doctor

For questions or comments, please visit: goldmountainbeauty.com

STOP USE

- If irritation occurs, discontinue use and consult a doctor

INDICATIONS AND USAGE

Trim nails and file the surface using an emery board
Apply a thin layer of product over affected areas twice daily (morning and night) especially around free edges of nails (under tips) and cuticles and the space around nails
Allow solution to soak into nail or skin
Application to adjacent nails is recommended to prevent the spread of infection
Keep affected areas clean and dry throughout the day
Supervise children in the use of this product

Warnings

For external use only

- Do not use on children under 2 years of age unless directed by a doctor
- Avoid contact with eyes, ears or mouth
- If irritation occurs, discontinue use and consult a doctor
- If swallowed, get medical help or consult a poison control center immediately.

Directions

- Trim nails and file the surface using an emery board
- Apply a thin layer of product over affected areas twice daily (morning and night) especially around free edges of nails (under tips) and cuticles and the space around nails
- Allow solution to soak into nail or skin
- Application to adjacent nails is recommended to prevent the spread of infection
- Keep affected areas clean and dry throughout the day
- Supervise children in the use of this product

PACKAGE LABEL

GOLD MOUNTAIN

Beauty

Foot Therapy

Antifungal

Fungal Nail Eliminator